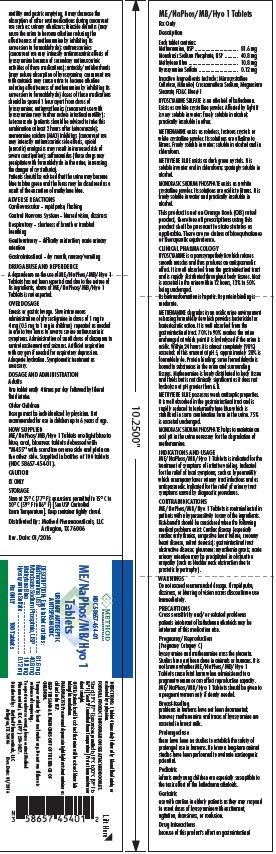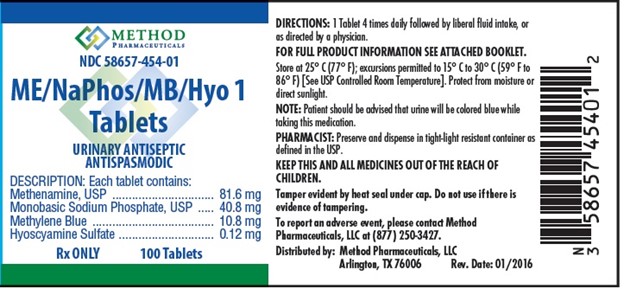 DRUG LABEL: Me NaPhos MB Hyo 1
NDC: 58657-454 | Form: TABLET
Manufacturer: Method Pharmaceuticals
Category: prescription | Type: HUMAN PRESCRIPTION DRUG LABEL
Date: 20251021

ACTIVE INGREDIENTS: METHENAMINE 81.6 mg/1 1; SODIUM PHOSPHATE, MONOBASIC, MONOHYDRATE 40.8 mg/1 1; METHYLENE BLUE ANHYDROUS 10.8 mg/1 1; HYOSCYAMINE SULFATE ANHYDROUS 0.12 mg/1 1
INACTIVE INGREDIENTS: CELLULOSE, MICROCRYSTALLINE; CROSCARMELLOSE SODIUM; MAGNESIUM STEARATE; FD&C BLUE NO. 1

Me-NaPhos-MB-Hyo 1 Tablets

Description

Each tablet contains:

Methenamine, USP ................................. 81.6 mg
Monobasic Sodium Phosphate, USP ......... 40.8 mg
Methylene Blue ....................................... 10.8 mg
Hyoscyamine Sulfate ............................... 0.12 mg

Inactive Ingredients include:

Microcrystalline
Cellulose, Mannitol, Croscarmellose Sodium, Magnesium
Stearate, FD&C Blue #1

HYOSCYAMINE SULFATE is an alkaloid of belladonna.
Exists as a white crystalline powder. Affected by light It
is very soluble in water; freely soluble in alcohol;
practically insoluble in ether.
METHENAMINE exists as colorless, lustrous crystals or
white crystalline powder. Its solutions are alkaline to
litmus. Freely soluble in water; soluble in alcohol and in
chloroform.

METHYLENE BLUE exists as dark green crystals. It is
soluble in water and in chloroform; sparingly soluble in
alcohol.

MONOBASIC SODIUM PHOSPHATE exists as a white
crystalline powder. Its solutions are acidic to litmus. It is
freely soluble in water and practically insoluble in
alcohol.

This product is not an Orange Book (OB) rated
product, therefore all prescriptions using this
product shall be pursuant to state statutes as
applicable. There are no claims of bioequivalence
or therapeutic equivalence.

CLINICAL PHARMACOLOGY

HYOSCYAMINE is a parasympatholytic which relaxes
smooth muscles and thus produces an antispasmodic
effect. It is well absorbed from the gastrointestinal tract
and is rapidly distributed throughout body tissues. Most
is excreted in the urine within 12 hours, 13% to 50%
being unchanged.

Its biotransformation is hepatic. Its protein binding is
moderate.

METHENAMINE degrades in an acidic urine environment
releasing formaldehyde which provides bactericidal or
bacteriostatic action. It is well absorbed from the
gastrointestinal tract. 70% to 90% reaches the urine
unchanged at which point it is hydrolyzed if the urine is
acidic. Within 24 hours it is almost completely (90%)
excreted; of this amount at pH 5, approximately 20% is
formaldehyde. Protein binding: some formaldehyde is
bound to substances in the urine and surrounding
tissues. Methenamine is freely distributed to body tissue
and fluids but is not clinically significant as it does not
hydrolyze at pH greater than 6.8.

METHYLENE BLUE possesses weak antiseptic properties.
It is well absorbed in the gastrointestinal tract and is
rapidly reduced to leukomethylene blue which is
stabilized in some combination form in the urine. 75%
is excreted unchanged.

MONOBASIC SODIUM PHOSPHATE helps to maintain an
acid pH in the urine necessary for the degradation of
methenamine.

INDICATION AND USAGE

ME/NaPhos/MB/Hyo 1 Tablets is indicated for the
treatment of symptoms of irritative voiding. Indicated
for the relief of local symptoms, such as hypermotility
which accompany lower urinary tract infections and as
antispasmodic. Indicated for the relief of urinary tract
symptoms caused by diagnostic procedures.

WARNINGS

Do not exceed recommended dosage. If rapid pulse,
dizziness, or blurring of vision occurs discontinue use
immediately.

PRECAUTIONS

(Pregnancy Category C)
hyoscyamine and methenamine cross the placenta.
Studies have not been done in animals or humans. It is
not known whether ME/NaPhos/MB/Hyo 1
Tablets cause fetal harm when administered to a
pregnant woman or can affect reproduction capacity.
ME/NaPhos/MB/Hyo 1 Tablets should be given to
a pregnant woman only if clearly needed.

Breast-feeding

problems in humans have not been documented;
however, methenamine and traces of hyoscyamine are
excreted in breast milk.

Prolonged use

there have been no studies to establish the safety of
prolonged use in humans. No known long-term animal
studies have been performed to evaluate carcinogenic
potential.

Pediatric

infants and young children are especially susceptible to
the toxic effect of the belladonna alkaloids.

Geriatric

use with caution in elderly patients as they may respond
to usual doses of hyoscyamine with excitement,
agitation, drowsiness, or confusion.

Drug Interactions

because of this product's effect on gastrointestinal

motility and gastric emptying, it may decrease the
absorption of other oral medications during concurrent
use such as: urinary alkalizers; thiazide diuretics (may
cause the urine to become alkaline reducing the
effectiveness of methenamine by inhibiting its
conversion to formaldehyde); antimuscarinics
(concurrent use may intensify antimuscarinic effects of
hyoscyamine because of secondary antimuscarinic
activities of these medications); antacids/antidiarrheals
(may reduce absorption of hyoscyamine, concurrent use
with antacids may cause urine to become alkaline
reducing effectiveness of methenamine by inhibiting its
conversion to formaldehyde) doses of these medications
should be spaced 1 hour apart from doses of
hyoscyamine; antimyasthenics (concurrent use with
hyoscyamine may further reduce intestinal motility);
ketoconazole (patients should be advised to take this
combination at least 2 hours after ketoconazole);
monoamine oxidase (MAO) Inhibitors (concurrent use
may intensify antimuscarinic side effects, opioid
(narcotic) analgesics may result in increased risk of
severe constipation); sulfonamides (these drugs may
precipitate with formaldehyde in the urine, increasing
the danger of crystalluria).
Patients should be advised that the urine may become
blue to blue green and the feces may be discolored as a
result of the excretion of methylene blue.

ADVERSE REACTIONS

Cardiovascular – rapid pulse, flushing

Central Nervous System – blurred vision, dizziness

Respiratory – shortness of breath or troubled
breathing

Genitourinary – difficulty micturition, acute urinary
retention

Gastrointestinal – dry mouth, nausea/vomiting

DRUG ABUSE AND DEPENDENCE

A dependence on the use of ME/NaPhos/MB/Hyo 1
Tablets has not been reported and due to the nature of
its ingredients, abuse of ME/NaPhos/MB/Hyo 1
Tablets is not expected.

OVERDOSAGE

Emesis or gastric lavage. Slow intravenous
administration of physostigmine in doses of 1 mg to
4 mg (0.5 mg to 1 mg in children), repeated as needed
in one to two hours to reverse severe antimuscarinic
symptoms. Administration of small doses of diazepam to
control excitement and seizures. Artificial respiration
with oxygen if needed for respiratory depression.
Adequate hydration. Symptomatic treatment as
necessary.

DOSAGE AND ADMINISTRATION

Adults

One tablet orally 4 times per day followed by liberal
fluid intake.

Older Children

Dosage must be individualized by physician. Not
recommended for use in children up to 6 years of age.

HOW SUPPLIED

ME/NaPhos/MB/Hyo 1 Tablets are light blue to
blue, oval, biconvex tablets debossed with
"M455" with scoreline on one side and plain on
the other side. Supplied in bottles of 100 tablets
(NDC 58657-454-01).

OTHER SAFETY INFORMATION

CAUTION

RX ONLY

STORAGE

Store at 25° C (77° F); excursions permitted to 15° C to
30° C (59° F to 86° F) [See USP Controlled
Room Temperature]. Keep container tightly closed.

Distributed By: Method Pharmaceuticals, LLC
Arlington, TX 76006

Rev. Date: 01/2016

GENERAL PRECAUTIONS

DIRECTIONS: 1 Tablet 4 times daily followed by liberal fluid intake, or
as directed by a physician.

FOR FULL PRODUCT INFORMATION SEE ATTACHED BOOKLET.
Store at 25° C (77° F); excursions permitted to 15° C to 30° C (59° F to
86° F) [See USP Controlled Room Temperature]. Protect from moisture or
direct sunlight.

NOTE: Patient should be advised that urine will be colored blue while
taking this medication.

PHARMACIST: Preserve and dispense in tight-light resistant container as
defined in the USP.

KEEP THIS AND ALL MEDICINES OUT OF THE REACH OF

CHILDREN.

Tamper evident by heat seal under cap. Do not use if there is
evidence of tampering.

To report an adverse event, please contact Method
Pharmaceuticals, LLC at (877) 250-3427.

PACKAGE LABEL

Distributed by: Method Pharmaceuticals, LLC
Arlington, TX 76006 Rev. Date: 01/2016

Pinciple Display Panel

Booklet